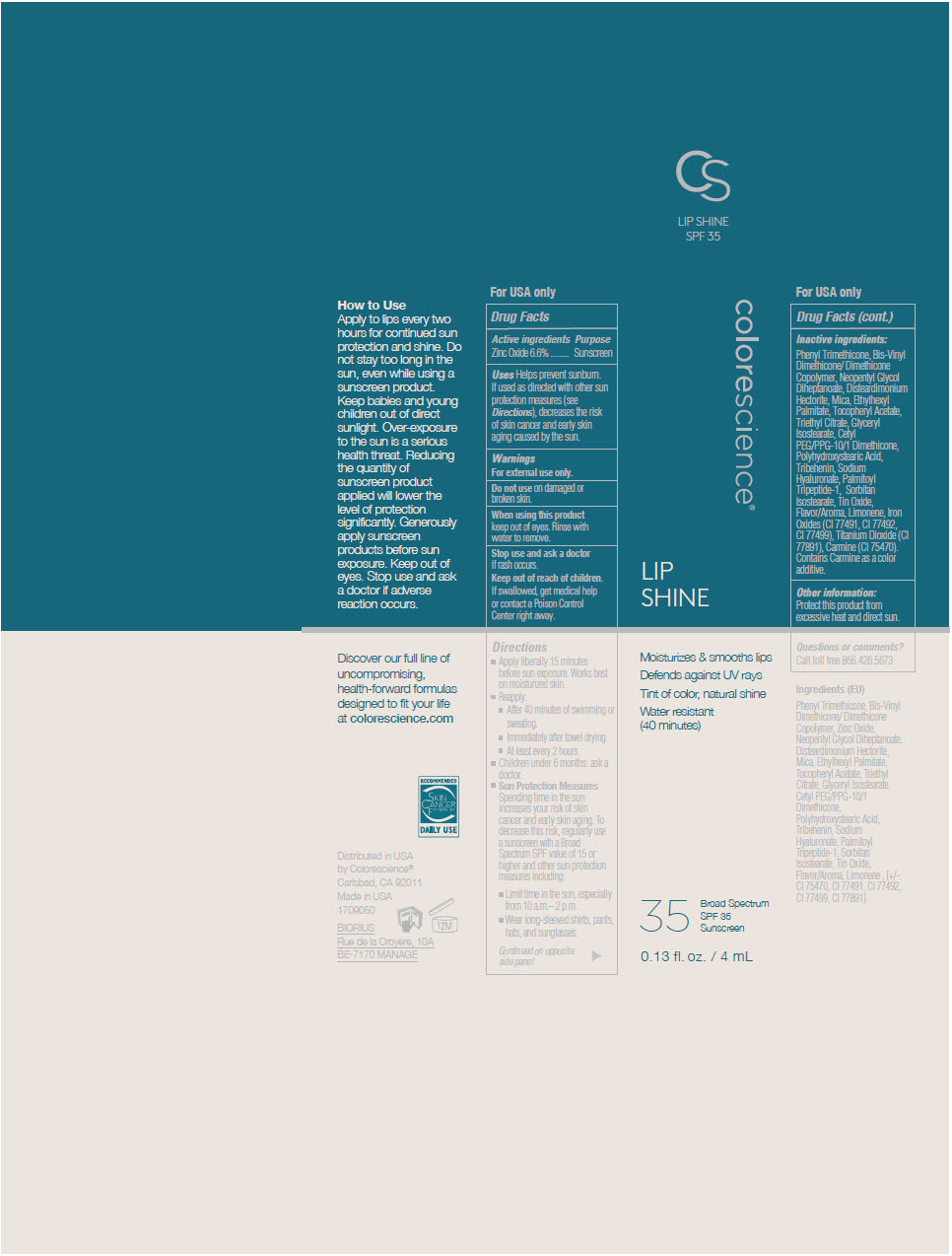 DRUG LABEL: Lip Shine SPF35 Sunscreen
NDC: 68078-028 | Form: LIQUID
Manufacturer: Colorescience
Category: otc | Type: HUMAN OTC DRUG LABEL
Date: 20241213

ACTIVE INGREDIENTS: Zinc Oxide 66 mg/1 mL
INACTIVE INGREDIENTS: Phenyl Trimethicone; Neopentyl Glycol Diheptanoate; Disteardimonium Hectorite; MICA; Ethylhexyl Palmitate; Triethyl Citrate; Glyceryl Isostearate; .ALPHA.-TOCOPHEROL ACETATE; CETYL PEG/PPG-10/1 DIMETHICONE (HLB 3); POLYHYDROXYSTEARIC ACID (2300 MW); Tribehenin; HYALURONATE SODIUM; Palmitoyl Tripeptide-1; Sorbitan Isostearate; LIMONENE, (+)-; STANNIC OXIDE; FERRIC OXIDE RED; FERROSOFERRIC OXIDE; FERRIC OXIDE YELLOW; CARMINIC ACID; TITANIUM DIOXIDE

Lip Shine SPF35 Sunscreen

Drug Facts

Active ingredients

Zinc Oxide 6.6%

Purpose

Sunscreen

Uses

Helps prevent sunburn. If used as directed with other sun protection measures (see Directions), decreases the risk of skin cancer and early skin aging caused by the sun.

Warnings

For external use only.

Do not use on damaged or broken skin.

When using this product keep out of eyes. Rinse with water to remove.

Stop use and ask a doctor if rash occurs.

Keep out of reach of children.

If swallowed, get medical help or contact a Poison Control Center right away.

Directions

- Apply liberally 15 minutes before sun exposure. Works best on moisturized skin.
- Reapply:
  - After 40 minutes of swimming or sweating.
  - Immediately after towel drying.
  - At least every 2 hours.
- Children under 6 months: ask a doctor.
- Sun Protection Measures
  Spending time in the sun increases your risk of skin cancer and early skin aging. To decrease this risk, regularly use a sunscreen with a Broad Spectrum SPF value of 15 or higher and other sun protection measures including:
  - Limit time in the sun, especially from 10 a.m.– 2 p.m.
  - Wear long-sleeved shirts, pants, hats, and sunglasses.

Inactive ingredients

Phenyl Trimethicone, Bis-Vinyl Dimethicone/ Dimethicone Copolymer, Neopentyl Glycol Diheptanoate, Disteardimonium Hectorite, Mica, Ethylhexyl Palmitate, Tocopheryl Acetate, Triethyl Citrate, Glyceryl Isostearate, Cetyl PEG/PPG-10/1 Dimethicone, Polyhydroxystearic Acid, Tribehenin, Sodium Hyaluronate, Palmitoyl Tripeptide-1, Sorbitan Isostearate, Tin Oxide, Flavor/Aroma, Limonene, Iron Oxides (CI 77491, CI 77492, CI 77499), Titanium Dioxide (CI 77891), Carmine (CI 75470). Contains Carmine as a color additive.

Other information

Protect this product from excessive heat and direct sun.

Questions or comments?

Call toll free 866.426.5673

Distributed in USA
by Colorescience®
Carlsbad, CA 92011

PRINCIPAL DISPLAY PANEL - 4 mL Tube Carton

colorescience®

LIP
SHINE

Moisturizes & smooths lips

Defends against UV rays

Tint of color, natural shine

Water resistant
(40 minutes)

35

Broad Spectrum
SPF 35
Sunscreen

0.13 fl. oz. / 4 mL